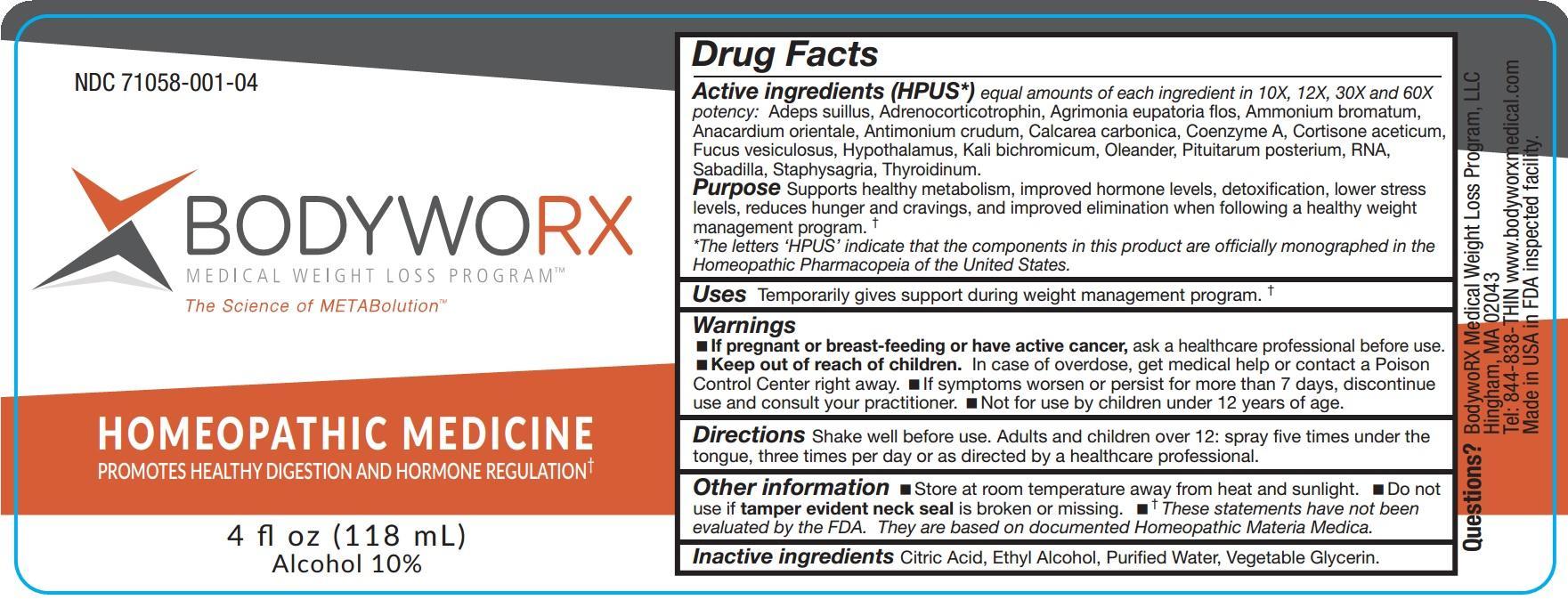 DRUG LABEL: BODYWORX
NDC: 71058-001 | Form: LIQUID
Manufacturer: BodywoRX Medical Weight Loss Program, LLC
Category: homeopathic | Type: HUMAN OTC DRUG LABEL
Date: 20170522

ACTIVE INGREDIENTS: LARD 10 [hp_X]/118 mL; CORTICOTROPIN 10 [hp_X]/118 mL; AGRIMONIA EUPATORIA FLOWER 10 [hp_X]/118 mL; AMMONIUM BROMIDE 10 [hp_X]/118 mL; SEMECARPUS ANACARDIUM JUICE 10 [hp_X]/118 mL; ANTIMONY TRISULFIDE 10 [hp_X]/118 mL; OYSTER SHELL CALCIUM CARBONATE, CRUDE 10 [hp_X]/118 mL; COENZYME A 10 [hp_X]/118 mL; CORTISONE ACETATE 10 [hp_X]/118 mL; FUCUS VESICULOSUS 10 [hp_X]/118 mL; BOS TAURUS HYPOTHALAMUS 10 [hp_X]/118 mL; POTASSIUM DICHROMATE 10 [hp_X]/118 mL; NERIUM OLEANDER LEAF 10 [hp_X]/118 mL; SUS SCROFA PITUITARY GLAND 10 [hp_X]/118 mL; SACCHAROMYCES CEREVISIAE RNA 10 [hp_X]/118 mL; SCHOENOCAULON OFFICINALE SEED 10 [hp_X]/118 mL; DELPHINIUM STAPHISAGRIA SEED 10 [hp_X]/118 mL; THYROID, UNSPECIFIED 10 [hp_X]/118 mL
INACTIVE INGREDIENTS: CITRIC ACID MONOHYDRATE; ALCOHOL; WATER; GLYCERIN

BodywoRX

ACTIVE INGREDIENT

Active ingredients (HPUS*) equal amounts of each ingredient in 10X, 12X, 30X and 60X potency:

Adeps suillus, Adrenocorticotrophin, Agrimonia eupatoria flos, Ammonium bromatum, Anacardium orientale, Antimonium crudum, Calcarea carbonica, Coenzyme A, Cortisone aceticum, Fucus vesiculosus, Hypothalamus, Kali bichromicum, Oleander, Pituitarum posterium, RNA, Sabadilla, Staphysagria, Thyroidinum.

Purpose

Supports healthy metabolism, improved hormone levels, detoxification, lower stress levels, reduces hunger and cravings, and improved elimination when following a healthy weight management program.†

*The letters 'HPUS' indicate that the components in this product are officially monographed in the Homeopathic Pharmacopeia of the United States.

Uses

Temporarily gives support during weight management program.†

Warnings

- If pregnant or breast-feeding or have active cancer, ask a healthcare professional before use.
- Keep out of the reach of children. In case of overdose, get medical help or contact a Poison Control Center right away.
- If symptoms worsen or persist for more than 7 days, discontinue use and consult your practitioner.
- Not for use by children under 12 years of age.

Keep out of the reach of children.

Directions

Shake well before use. Adults and children over 12: spray five times under the tongue, three times per day or as directed by a healthcare professional.

Other information

- Store at room temperature away from heat and sunlight.
- Do not use if tamper evident neck seal is broken or missing.
- †These statements have not been evaluated by the FDA. They are based on documented Homeopathic Materia Medica.

Inactive ingredients

Citric Acid, Ethyl Alcohol, Purified Water, Vegetable Glycerin.

Questions?

BodywoRX Medical Weight Loss Program, LLC

Hingham, MA 02043

Tel: 844-838-THIN

www.bodyworxmedical.com

Made in USA in FDA inspected facility.

PURPOSE

Promotes Healthy Digestion and Hormone Regulation†

PACKAGE LABEL

NDC 71058-001-04

BODYWORX

Medical Weight Loss Program™

The Science of METABolution™

HOMEOPATHIC MEDICINE

PROMOTES HEALTHY DIGESTION AND HORMONE REGULATION†

4 fl oz (118 mL)

Alcohol 10%